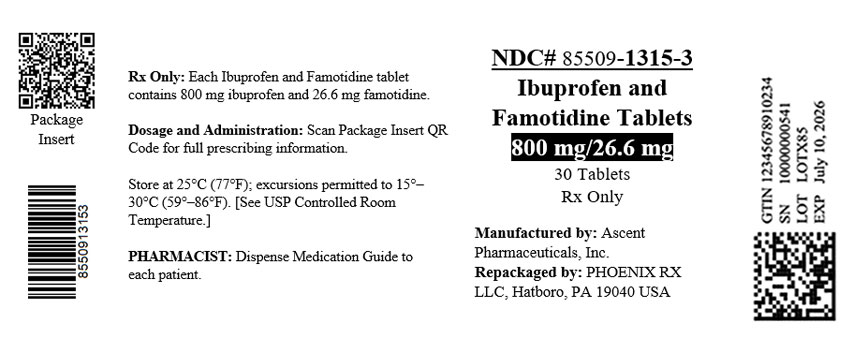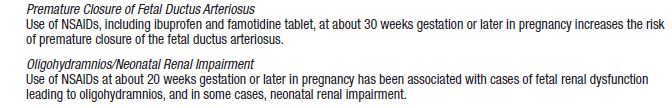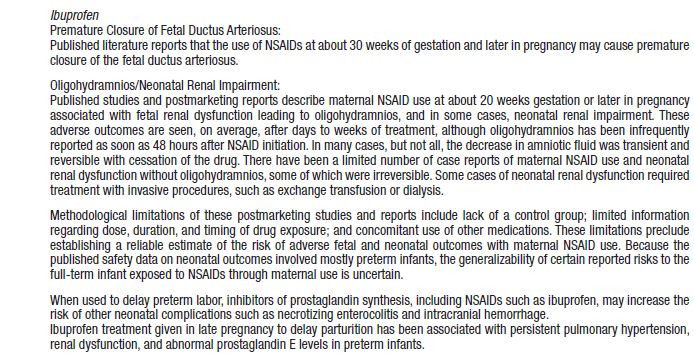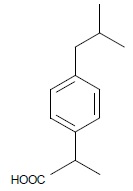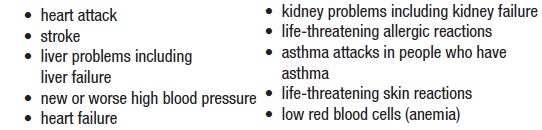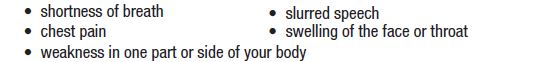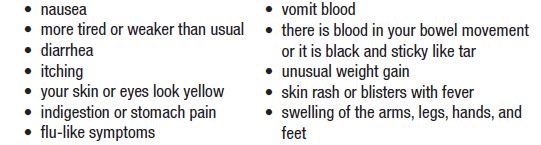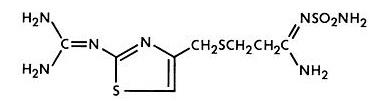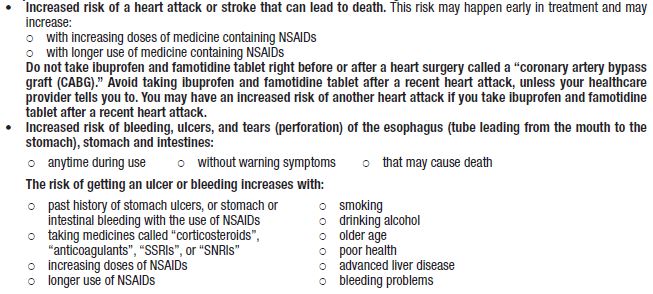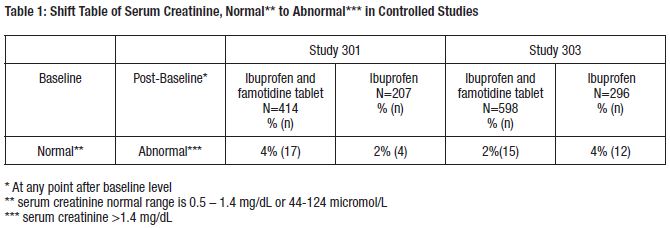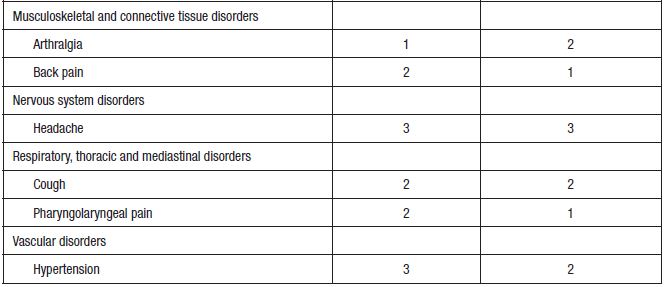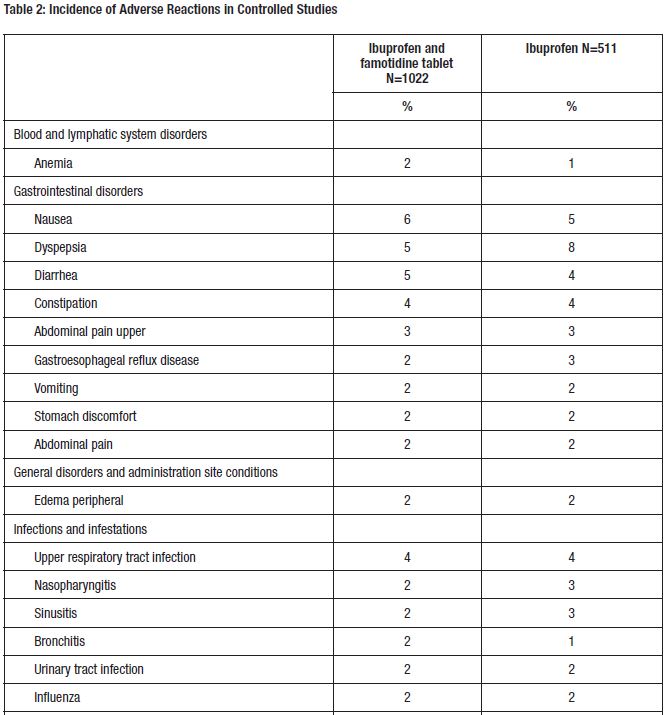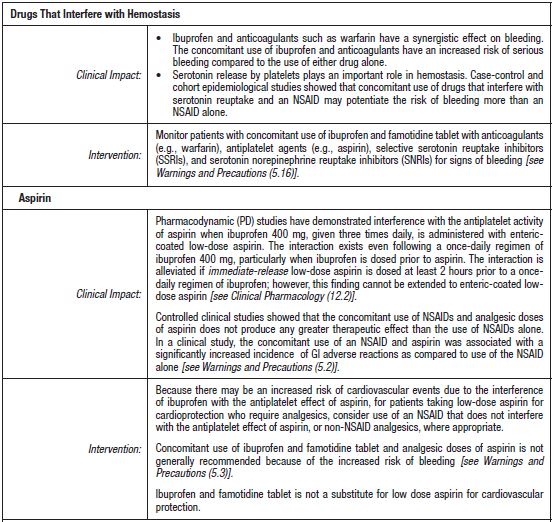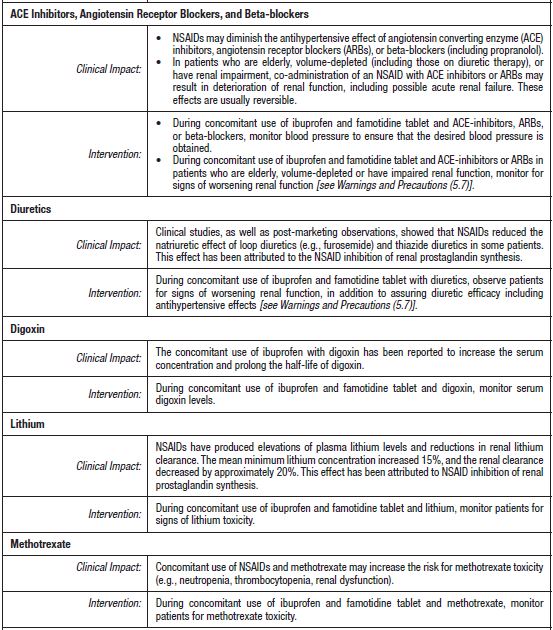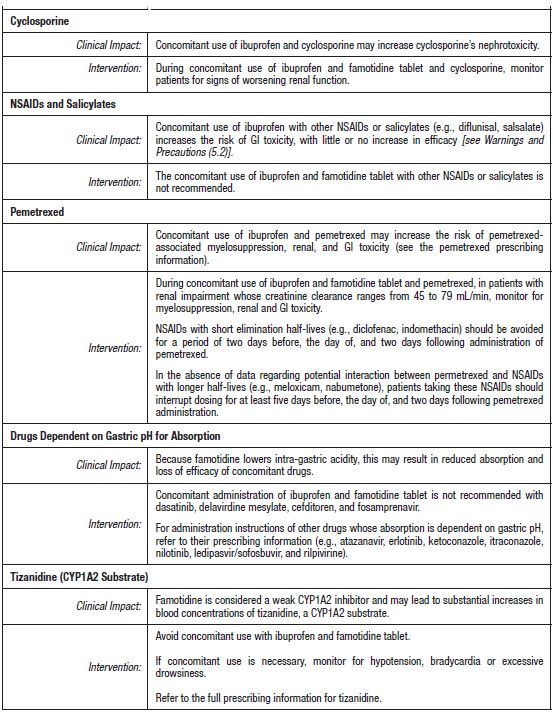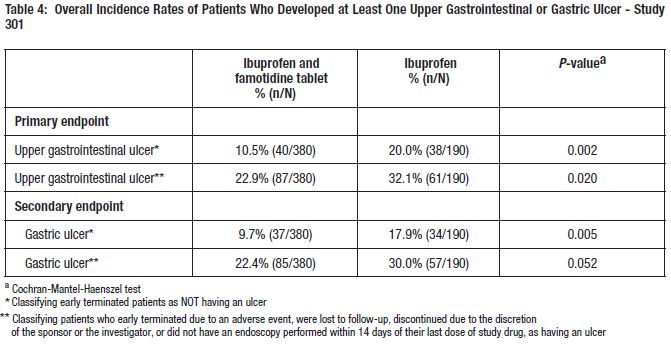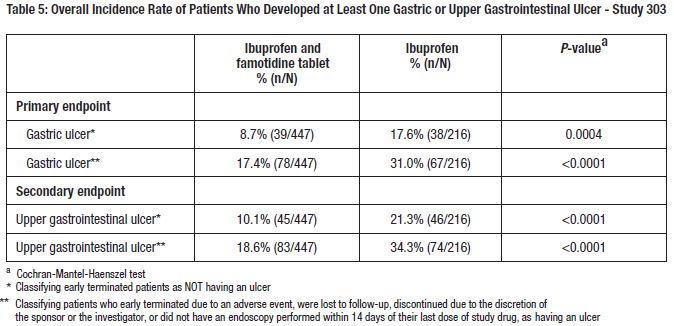 DRUG LABEL: IBUPROFEN AND FAMOTIDINE
NDC: 85509-1315 | Form: TABLET
Manufacturer: PHOENIX RX LLC
Category: prescription | Type: HUMAN PRESCRIPTION DRUG LABEL
Date: 20251015

ACTIVE INGREDIENTS: IBUPROFEN 800 mg/1 1; FAMOTIDINE 26.6 mg/1 1
INACTIVE INGREDIENTS: MICROCRYSTALLINE CELLULOSE; STARCH, CORN; SILICON DIOXIDE; MAGNESIUM STEARATE; HYDROXYPROPYL CELLULOSE, UNSPECIFIED; GLYCERIN; CROSCARMELLOSE SODIUM; FD&C BLUE NO. 1; TALC; POVIDONE; FD&C BLUE NO. 2

HIGHLIGHTS OF PRESCRIBING INFORMATION

These highlights do not include all the information needed to use IBUPROFEN and FAMOTIDINE TABLETS safely and effectively. See full prescribing information for IBUPROFEN and FAMOTIDINE TABLETS.
IBUPROFEN and FAMOTIDINE tablets, for oral use
Initial U.S. Approval: 2011

WARNING: RISK OF SERIOUS CARDIOVASCULAR AND GASTROINTESTINAL EVENTS

WARNING: RISKOFSERIOUS CARDIOVASCULAR AND GASTROINTESTINAL EVENTS

See full prescribing informationfor complete boxed warning.

- Nonsteroidal anti-inflammatory drugs (NSAIDs) cause an increased risk of serious cardiovascular thrombotic events, including myocardial infarction and stroke, which can be fatal. This risk may occur early in treatment and may increase with duration of use (5.1)
- Ibuprofen and famotidine tablet is contraindicated in the setting of coronary artery bypass graft (CABG) surgery (4, 5.1)
- NSAIDs causean increased risk of serious gastrointestinal (GI) adverse events including bleeding, ulceration, and perforation of the stomach or intestines, which can be fatal. These events can occur at any time during use and without warning symptoms. Elderly patients and patients with a prior history of peptic ulcer disease and/or GI bleeding are at greater risk for serious GI events (5.2)

RECENT MAJOR CHANGES

- Warnings and Precautions, Serious Skin Reactions (5.11) 07/2024
- Warnings and Precautions, Drug Reaction with Eosinophilia and Systemic Symptoms (DRESS) (5.12) 04/2021
- Warnings and Precautions, Fetal Toxicity (5.13) 04/2021

1 INDICATIONS AND USAGE

Ibuprofen and famotidine tablet, a combination of a nonsteroidal anti-inflammatory drug (NSAID) ibuprofen and the histamine H2-receptor antagonist famotidine, is indicated for the relief of signs and symptoms of rheumatoid arthritis and osteoarthritis and to decrease the risk of developing upper gastrointestinal ulcers, which in the clinical trials was defined as a gastric and/or duodenal ulcer, in patients who are taking ibuprofen for those indications. The clinical trials primarily enrolled patients less than 65 years of age without a prior history of gastrointestinal ulcer. Controlled trials do not extend beyond 6 months. (1)

2 DOSAGE AND ADMINISTRATION

- One ibuprofen and famotidine tablet administered orally three times per day. (2)
- Use ibuprofen at the lowest effective dosage for the shortest duration consistent with individual patient treatment goals. (2)
- Do not substitute ibuprofen and famotidine tablet with the single-ingredient products of ibuprofen and famotidine. (2)

3 DOSAGE FORMS AND STRENGTHS

- Ibuprofen and Famotidine Tablets: 800 mg ibuprofen and 26.6 mg famotidine. (3)

4 CONTRAINDICATIONS

- Known hypersensitivity to ibuprofen or famotidine or any components of the drug product. (4)
- History of asthma, urticaria, or allergic-type reactions after taking aspirin or other NSAIDs. (4)
- In the setting of CABG surgery. (4)
- Known hypersensitivity to other H2-receptor antagonists. (4)

5 WARNINGS AND PRECAUTIONS

• Hepatotoxicity: Inform patients of warning signs and symptoms of hepatotoxicity. Discontinue if abnormal liver tests persist or worsen or if clinical signs and symptoms of liver disease develop. (5.4)
• Hypertension: Patients taking some antihypertensive medications may have impaired response to these therapies when taking NSAIDs. Monitor blood pressure. (5.5, 7)
• Heart Failure and Edema: Avoid use of ibuprofen and famotidine tablets in patients with severe heart failure unless benefits are expected to outweigh risk of worsening heart failure. (5.6)
• Active Bleeding: Active and clinically significant bleeding from any source can occur; discontinue ibuprofen and famotidine tablet if active bleeding occurs. (5.3)
• Renal Toxicity: Monitor renal function in patients with renal or hepatic impairment, heart failure, dehydration, or hypovolemia. Avoid use of ibuprofen and famotidine tablet in patients with advanced renal disease unless benefits are expected to outweigh risk of worsening renal function. (5.7)
• Anaphylactic Reactions: Seek emergency help if an anaphylactic reaction occurs. (5.8)
• Exacerbation of Asthma Related to Aspirin Sensitivity: Ibuprofen and famotidine tablet is contraindicated in patients with aspirin-sensitive asthma. Monitor patients with preexisting asthma (without aspirin-sensitivity). (5.10)
• Serious Skin Reactions: Discontinue ibuprofen and famotidine tablet at first appearance of skin rash or other signs of hypersensitivity (5.11).
• Drug Reaction with Eosinophilia and Systematic Symptoms (DRESS):Discontinue and evaluate clinically (5.12).
• Fetal Toxicity: Limit use of NSAIDs, including ibuprofen and famotidine tablet, between about 20 to 30 weeks in pregnancy due to the risk of oligohydramnios/fetal renal dysfunction. Avoid use of NSAIDs in women at about 30 weeks gestation and later in pregnancy due to the risks of oligohydramnios/fetal renal dysfunction and premature closure of the fetal ductus arteriosus (5.13, 8.1)
• Hematologic Toxicity: Monitor hemoglobin or hematocrit in patient with any signs or symptoms of anemia. (5.14)

6 ADVERSE REACTIONS

Most common adverse reactions (≥1% and greater than ibuprofen alone) are nausea, diarrhea, constipation, upper abdominal pain, and headache. (6.1)

To report SUSPECTED ADVERSE REACTIONS, contact Camber Pharmaceuticals, Inc., at 1-866-495-8330 or FDA at 1-800-FDA-1088 or www.fda.gov/medwatch

7 DRUG INTERACTIONS

See full prescribing information for a list of clinically important drug interactions. (7)

8 USE IN SPECIFIC POPULATIONS

- Pregnancy: Use of NSAIDs during the third trimester of pregnancy increases the risk of premature closure of the fetal ductus arteriosus. Avoid use of NSAIDs in pregnant women starting at 30 weeks gestation. (5.13, 8.1)
- Femalesand Males of Reproductive Potential: NSAIDs are associated with reversible infertility. Consider withdrawal of ibuprofen and famotidine tablet in women who have difficulties conceiving. (8.3)

FULL PRESCRIBING INFORMATION

WARNING: RISK OF SERIOUS CARDIOVASCULAR AND GASTROINTESTINAL EVENTS

Cardiovascular Thrombotic Events

- Nonsteroidal anti-inflammatory drugs (NSAIDs) cause an increased risk of serious cardiovascular thrombotic events, including myocardial infarction and stroke, which can be fatal. This risk may occur early in treatment and may increase with duration of use [see Warnings and Precautions (5.1)].
- Ibuprofen and famotidine tablet is contraindicated in the setting of coronary artery bypass graft (CABG) surgery [see Contraindications (4) and Warnings and Precautions (5.1)].

Gastrointestinal Bleeding, Ulceration, and Perforation

- NSAIDs cause an increased risk of serious gastrointestinal (GI) adverse events including bleeding, ulceration, and perforation of the stomach or intestines, which can be fatal. These events can occur at any time during use and without warning symptoms. Elderly patients and patients with a prior history of peptic ulcer disease and/or GI bleeding are at greater risk for serious GI events [see Warnings and Precautions (5.2)].

1 INDICATIONS AND USAGE

Ibuprofen and famotidine tablet, a combination of the NSAID ibuprofen and the histamine H2-receptor antagonist famotidine, is indicated for the relief of signs and symptoms of rheumatoid arthritis and osteoarthritis and to decrease the risk of developing upper gastrointestinal ulcers, which in the clinical trials was defined as a gastric and/or duodenal ulcer, in patients who are taking ibuprofen for those indications. The clinical trials primarily enrolled patients less than 65 years of age without a prior history of gastrointestinal ulcer. Controlled trials do not extend beyond 6 months [see Clinical Studies (14), Use in Specific Populations (8.5)].

2 DOSAGE AND ADMINISTRATION

Carefully consider the potential benefits and risks of ibuprofen and famotidine tablets and other treatment options before deciding to use ibuprofen and famotidine tablets. Use ibuprofen at the lowest effective dosage for the shortest duration consistent with individual patient treatment goals [see Warnings and Precautions (5)].

The recommended daily dose of ibuprofen and famotidine 800 mg/26.6 mg is a single tablet administered orally three times per day.

Ibuprofen and famotidine tablets should be swallowed whole, and should not be cut to supply a lower dose. Do not chew, divide, or crush tablets.

Patients should be instructed that if a dose is missed, it should be taken as soon possible. However, if the next scheduled dose is due, the patient should not take the missed dose, and should be instructed to take the next dose on time. Patients should be instructed not to take 2 doses at one time to make up for a missed dose.

Do not substitute ibuprofen and famotidine tablet with the single-ingredient products of ibuprofen and famotidine.

3 DOSAGE FORMS AND STRENGTHS

Ibuprofen and famotidine tablets: 800 mg/26.6 mg, are Blue/Light blue coated Modified Oval shaped tablets debossed with T396 on one side and an engraved circle on the other side.

4 CONTRAINDICATIONS

Ibuprofen and famotidine tablet is contraindicated in the following patients:

- Known hypersensitivity (e.g., anaphylactic reactions and serious skin reactions) to ibuprofen or famotidine or any components of the drug product [see Warnings and Precautions (5.8, 5.11)].
- History of asthma, urticaria, or other allergic-type reactions after taking aspirin or other NSAIDs. Severe, sometimes fatal, anaphylactic reactions to NSAIDs have been reported in such patients [see Warnings and Precautions (5.8, 5.10)].
- In the setting of coronary artery bypass graft (CABG) surgery [see Warnings and Precautions (5.1)].
- Ibuprofen and famotidine tablet should not be administered to patients with a history of hypersensitivity to other H2-receptor antagonists. Cross sensitivity with other H2-receptor antagonists has been observed.

5 WARNINGS AND PRECAUTIONS

5.1 Cardiovascular Thrombotic Events

Clinical trials of several COX-2 selective and nonselective NSAIDs of up to three years duration have shown an increased risk of serious cardiovascular (CV) thrombotic events, including myocardial infarction (MI), and stroke, which can be fatal. Based on available data, it is unclear that the risk for CV thrombotic events is similar for all NSAIDs. The relative increase in serious CV thrombotic events over baseline conferred by NSAID use appears to be similar in those with and without known CV disease or risk factors for CV disease. However, patients with known CV disease or risk factors had a higher absolute incidence of excess serious CV thrombotic events, due to their increased baseline rate. Some observational studies found that this increased risk of serious CV thrombotic events began as early as the first weeks of treatment. The increase in CV thrombotic risk has been observed most consistently at higher doses.

To minimize the potential risk for an adverse CV event in NSAID-treated patients, use the lowest effective dose for the shortest duration possible. Physicians and patients should remain alert for the development of such events, throughout the entire treatment course, even in the absence of previous CV symptoms. Patients should be informed about the symptoms of serious CV events and the steps to take if they occur.

There is no consistent evidence that concurrent use of aspirin mitigates the increased risk of serious CV thrombotic events associated with NSAID use. The concurrent use of aspirin and an NSAID, such as ibuprofen, increases the risk of serious gastrointestinal GI events [see Warnings and Precautions (5.2)].

Status Post Coronary Artery Bypass Graft (CABG) Surgery

Two large, controlled, clinical trials of a COX-2 selective NSAID for the treatment of pain in the first 10–14 days following CABG surgery found an increased incidence of myocardial infarction and stroke. NSAIDs are contraindicated in the setting of CABG [see Contraindications (4)].

Post-MI Patients

Observational studies conducted in the Danish National Registry have demonstrated that patients treated with NSAIDs in the post-MI period were at increased risk of reinfarction, CV-related death, and all-cause mortality beginning in the first week of treatment. In this same cohort, the incidence of death in the first year post-MI was 20 per 100 person years in NSAID-treated patients compared to 12 per 100 person years in non-NSAID exposed patients. Although the absolute rate of death declined somewhat after the first year post-MI, the increased relative risk of death in NSAID users persisted over at least the next four years of follow-up.

Avoid the use of ibuprofen and famotidine tablet in patients with a recent MI unless the benefits are expected to outweigh the risk of recurrent CV thrombotic events. If ibuprofen and famotidine tablet is used in patients with a recent MI, monitor patients for signs of cardiac ischemia.

5.2 Gastrointestinal Bleeding, Ulceration, and Perforation

NSAIDs, including ibuprofen, cause serious gastrointestinal (GI) adverse events including inflammation, bleeding, ulceration, and perforation of the esophagus, stomach, small intestine, or large intestine, which can be fatal. These serious adverse events can occur at any time, with or without warning symptoms, in patients treated with NSAIDs. Only one in five patients who develop a serious upper GI adverse event on NSAID therapy is symptomatic. Upper GI ulcers, gross bleeding, or perforation caused by NSAIDs occurred in approximately 1% of patients treated for 3-6 months, and in about 2%-4% of patients treated for one year. However, even short-term NSAID therapy is not without risk.

Risk Factors for GI Bleeding, Ulceration, and Perforation

Patients with a prior history of peptic ulcer disease and/or GI bleeding who used NSAIDs had a greater than 10-fold increased risk for developing a GI bleed compared to patients without these risk factors. Other factors that increase the risk of GI bleeding in patients treated with NSAIDs include longer duration of NSAID therapy; concomitant use of oral corticosteroids, aspirin, anticoagulants, or selective serotonin reuptake inhibitors (SSRIs); smoking; use of alcohol; older age; and poor general health status. Most postmarketing reports of fatal GI events occurred in elderly or debilitated patients. Additionally, patients with advanced liver disease and/or coagulopathy are at increased risk for GI bleeding.

NSAIDs should be given with care to patients with a history of inflammatory bowel disease (ulcerative colitis, Crohn’s disease) as their condition may be exacerbated.

Strategiesto Minimize the GI Risks in NSAID-treated patients:

- Use the lowest effective dosage for the shortest possible duration.
- Avoid administration of more than one NSAID at a time.
- Avoid use in patients at higher risk unless benefits are expected to outweigh the increased risk of bleeding. For such patients, as well as those with active GI bleeding, consider alternate therapies other than NSAIDs.
- Remain alert for signs and symptoms of GI ulceration and bleeding during NSAID therapy.
- If a serious GI adverse event is suspected, promptly initiate evaluation and treatment, and discontinue ibuprofen and famotidine tablet until a serious GI adverse event is ruled out.
- In the setting of concomitant use of low-dose aspirin for cardiac prophylaxis, monitor patients more closely for evidence of GI bleeding [see Drug Interactions (7)].

5.3 Active Bleeding

When active and clinically significant bleeding from any source occurs in patients receiving ibuprofen and famotidine tablet, the treatment should be withdrawn. Patients with initial hemoglobin values of 10 g or less who are to receive long-term therapy should have hemoglobin values determined periodically.

5.4 Hepatotoxicity

Elevations of ALT or AST (three or more times the upper limit of normal [ULN]) have been reported in approximately 1% of NSAID-treated patients in clinical trials. In addition, rare, sometimes fatal, cases of severe hepatic injury, including fulminant hepatitis, liver necrosis, and hepatic failure have been reported.

Elevations of ALT or AST (less than three times ULN) may occur in up to 15% of patients treated with NSAIDs including ibuprofen.

Inform patients of the warning signs and symptoms of hepatotoxicity (e.g., nausea, fatigue, lethargy, diarrhea, pruritus, jaundice, right upper quadrant tenderness, and “flu-like” symptoms). If clinical signs and symptoms consistent with liver disease develop, or if systemic manifestations occur (e.g., eosinophilia, rash, etc.), discontinue ibuprofen and famotidine tablet immediately, and perform a clinical evaluation of the patient.

5.5 Hypertension

NSAIDs, including ibuprofen and famotidine tablet, can lead to new onset of hypertension or worsening of pre-existing hypertension, either of which may contribute to the increased incidence of CV events. Patients taking angiotensin converting enzyme (ACE) inhibitors, thiazide diuretics, or loop diuretics may have impaired response to these therapies when taking NSAIDs [see Drug Interactions (7)].

Monitor blood pressure (BP) during the initiation of NSAID treatment and throughout the course of therapy.

5.6 Heart Failure and Edema

The Coxib and traditional NSAID Trialists’ Collaboration meta-analysis of randomized controlled trials demonstrated an approximately two-fold increase in hospitalizations for heart failure in COX-2 selective treated patients and nonselective NSAID-treated patients compared to placebo-treated patients. In a Danish National Registry study of patients with heart failure, NSAID use increased the risk of MI, hospitalization for heart failure, and death.

Additionally, fluid retention and edema have been observed in some patients treated with NSAIDs. Use of ibuprofen may blunt the CV effects of several therapeutic agents used to treat these medical conditions (e.g., diuretics, ACE inhibitors, or angiotensin receptor blockers [ARBs]) [see Drug Interactions (7)].

Avoid the use of ibuprofen and famotidine tablet in patients with severe heart failure unless the benefits are expected to outweigh the risk of worsening heart failure. If ibuprofen and famotidine tablet is used in patients with severe heart failure, monitor patients for signs and symptoms of worsening heart failure.

5.7 Renal Toxicity and Hyperkalemia

Renal Toxicity

Long-term administration of NSAIDs has resulted in renal papillary necrosis and other renal injury. Renal toxicity has also been seen in patients in whom renal prostaglandins have a compensatory role in the maintenance of renal perfusion. In these patients, administration of an NSAID may cause a dose-dependent reduction in prostaglandin formation and, secondarily, in renal blood flow, which may precipitate overt renal decompensation. Patients at greatest risk of this reaction are those with impaired renal function, dehydration, hypovolemia, heart failure, liver dysfunction, those taking diuretics and ACE-inhibitors or ARBs, and the elderly. Discontinuation of NSAID therapy was usually followed by recovery to the pretreatment state.

No information is available from controlled clinical studies regarding the use of ibuprofen and famotidine tablet in patients with advanced renal disease. The renal effects of ibuprofen and famotidine tablet may hasten the progression of renal dysfunction in patients with pre-existing renal disease.

Correct volume status in dehydrated or hypovolemic patients prior to initiating ibuprofen and famotidine tablet. Monitor renal function in patients with renal or hepatic impairment, heart failure, dehydration, or hypovolemia during use of ibuprofen and famotidine tablet [see Drug Interactions (7)]. Avoid the use of ibuprofen and famotidine tablet in patients with advanced renal disease unless the benefits are expected to outweigh the risk of worsening renal failure. If ibuprofen and famotidine tablet is used in patients with advanced renal disease, monitor patients for signs of worsening renal function.

Hyperkalemia

Increases in serum potassium concentration, including hyperkalemia, have been reported with use of NSAIDs, even in some patients without renal impairment. In patients with normal renal function, these effects have been attributed to a hyporeninemic-hypoaldosteronism state.

5.8 Anaphylactic Reactions

Ibuprofen has been associated with anaphylactic reactions in patients with and without known hypersensitivity to ibuprofen and in patients with aspirin-sensitive asthma [see Contraindications (4), Warnings and Precautions (5.8)].

Seek emergency help if an anaphylactic reaction occurs.

5.9 Seizures

Central nervous system (CNS) adverse effects including seizures, delirium, and coma have been reported with famotidine in patients with moderate (creatinine clearance <50 mL/min) and severe renal insufficiency (creatinine clearance <10 mL/min), and the dosage of the famotidine component in ibuprofen and famotidine tablet is fixed. Therefore, ibuprofen and famotidine tablet is not recommended in patients with creatinine clearance < 50 mL/min.

5.10 Exacerbation of Asthma Related to Aspirin Sensitivity

A subpopulation of patients with asthma may have aspirin-sensitive asthma which may include chronic rhinosinusitis complicated by nasal polyps; severe, potentially fatal bronchospasm; and/or intolerance to aspirin and other NSAIDs. Because cross-reactivity between aspirin and other NSAIDs has been reported in such aspirin-sensitive patients, ibuprofen and famotidine tablet is contraindicated in patients with this form of aspirin sensitivity [see Contraindications (4)]. When ibuprofen and famotidine tablet is used in patients with preexisting asthma (without known aspirin sensitivity), monitor patients for changes in the signs and symptoms of asthma.

5.11 Serious Skin Reactions

NSAIDs, including ibuprofen, which is a component of ibuprofen and famotidine tablets, can cause serious skin adverse reactions such as exfoliative dermatitis, Stevens-Johnson Syndrome (SJS), and toxic epidermal necrolysis (TEN), which can be fatal. NSAIDs can also cause fixed drug eruption (FDE). FDE may present as a more severe variant known as generalized bullous fixed drug eruption (GBFDE), which can be life-threatening. These serious events may occur without warning. Inform patients about the signs and symptoms of serious skin reactions and to discontinue the use of ibuprofen and famotidine tablet at the first appearance of skin rash or any other sign of hypersensitivity. Ibuprofen and famotidine tablet is contraindicated in patients with previous serious skin reactions to NSAIDs [see Contraindications (4)].

5.12 Drug Reaction with Eosinophilia and Systemic Symptoms (DRESS)

Drug Reaction with Eosinophilia and Systemic Symptoms (DRESS) has been reported in patients taking NSAIDs such as ibuprofen and famotidine tablet. Some of these events have been fatal or life-threatening. DRESS typically, although not exclusively, presents with fever, rash, lymphadenopathy, and/or facial swelling. Other clinical manifestations may include hepatitis, nephritis, hematological abnormalities, myocarditis, or myositis. Sometimes symptoms of DRESS may resemble an acute viral infection. Eosinophilia is often present. Because this disorder is variable in its presentation, other organ systems not noted here may be involved. It is important to note that early manifestations of hypersensitivity, such as fever or lymphadenopathy, may be present even though rash is not evident. If such signs or symptoms are present, discontinue ibuprofen and famotidine tablet and evaluate the patient immediately.

5.13 Fetal Toxicity

Premature Closure of Fetal Ductus Arteriosus:

Avoid use of NSAIDs, including ibuprofen and famotidine tablet, in pregnant women at about 30 weeks gestation and later. NSAIDs, including ibuprofen and famotidine tablet, increase the risk of premature closure of the fetal ductus arteriosus at approximately this gestational age.

Oligohydramnios/Neonatal Renal Impairment:

Use of NSAIDs, including ibuprofen and famotidine tablet, at about 20 weeks gestation or later in pregnancy may cause fetal renal dysfunction leading to oligohydramnios and, in some cases, neonatal renal impairment. These adverse outcomes are seen, on average, after days to weeks of treatment, although oligohydramnios has been infrequently reported as soon as 48 hours after NSAID initiation. Oligohydramnios is often, but not always, reversible with treatment discontinuation. Complications of prolonged oligohydramnios may, for example, include limb contractures and delayed lung maturation. In some postmarketing cases of impaired neonatal renal function, invasive procedures such as exchange transfusion or dialysis were required.

If NSAID treatment is necessary between about 20 weeks and 30 weeks gestation, limit ibuprofen and famotidine tablet use to the lowest effective dose and shortest duration possible. Consider ultrasound monitoring of amniotic fluid if ibuprofen and famotidine tablet treatment is needed for a pregnant woman. Discontinue ibuprofen and famotidine tablet if oligohydramnios occurs and follow up according to clinical practice [see Use in Specific Populations (8.1)].

5.14 Hematologic Toxicity

Anemia has occurred in NSAID-treated patients. This may be due to occult or gross blood loss, fluid retention, or an incompletely described effect on erythropoiesis. If a patient treated with ibuprofen and famotidine tablet has any signs or symptoms of anemia, monitor hemoglobin or hematocrit.

NSAIDs, including ibuprofen and famotidine tablet, may increase the risk of bleeding events. Co-morbid conditions such as coagulation disorders or concomitant use of warfarin, and other anticoagulants, antiplatelet agents (e.g., aspirin), serotonin reuptake inhibitors (SSRIs) and serotonin norepinephrine reuptake inhibitors (SNRIs) may increase the risk. Monitor these patients for signs of bleeding [see Drug Interactions (7)].

5.15 Masking of Inflammation and Fever

The pharmacological activity of ibuprofen and famotidine tablet in reducing inflammation, and possibly fever, may diminish the utility of diagnostic signs in detecting infections.

5.16 Laboratory Monitoring

Because serious GI bleeding, hepatotoxicity, and renal injury can occur without warning symptoms or signs, consider monitoring patients on long-term NSAID treatment with a CBC and chemistry profile periodically [see Warnings and Precautions (5.2, 5.4, 5.7)].

5.17 Concomitant NSAID Use

Ibuprofen and famotidine tablet contains ibuprofen as one of its active ingredients. It should not be used with other ibuprofen-containing products.

The concomitant use of NSAIDs, including aspirin, with ibuprofen and famotidine tablet may increase the risk of adverse reactions [see Adverse Reactions (6), Drug Interactions (7), Clinical Studies (14)] .

5.18 Aseptic Meningitis

Aseptic meningitis with fever and coma has been observed on rare occasions in patients on ibuprofen, which is a component of ibuprofen and famotidine tablet. Although it is probably more likely to occur in patients with systemic lupus erythematosus (SLE) and related connective tissue diseases, it has been reported in patients who do not have an underlying chronic disease. If signs or symptoms of meningitis develop in a patient on ibuprofen and famotidine tablet, the possibility of its being related to ibuprofen should be considered.

5.19 Ophthalmological Effects

Blurred and/or diminished vision, scotomata, and/or changes in color vision have been reported. If a patient develops such complaints while receiving ibuprofen and famotidine tablet, the drug should be discontinued, and the patient should have an ophthalmologic examination which includes central visual fields and color vision testing.

6 ADVERSE REACTIONS

The following serious adverse reactions are discussed in greater detail in other sections of the labeling:

- Cardiovascular Thrombotic Events [see Warningsand Precautions (5.1)]
- GI Bleeding, Ulceration, and Perforation [see Warnings and Precautions (5.2)]
- Hepatotoxicity [see Warningsand Precautions (5.4)]
- Hypertension [see Warnings and Precautions (5.5)]
- Heart Failure and Edema [see Warnings and Precautions (5.6)]
- Renal Toxicity and Hyperkalemia [see Warnings and Precautions (5.7)]
- Anaphylactic Reactions [see Warnings and Precautions (5. 8)]
- Seizures [see Warnings and Precautions (5.9)]
- Serious Skin Reactions [see Warnings and Precautions (5.11)]
- Drug Reaction with Eosinophilia and Systemic Symptoms (DRESS) [see Warningsand Precautions (5.12)]
- Fetal Toxicity [see Warningsand Precautions (5.13)]
- Hematologic Toxicity [see Warnings and Precautions (5.14)]
- Aseptic Meningitis [see Warnings and Precautions (5.18)]
- Ophthalmological Effects [see Warningsand Precautions (5.19)]

6.1 Clinical Trials Experience

Because clinical trials are conducted under widely varying conditions, adverse reaction rates observed in the clinical trials of a drug cannot be directly compared to rates in the clinical trials of another drug and may not reflect the rates observed in practice.

The safety of ibuprofen and famotidine tablet was evaluated in 1022 patients in controlled clinical studies, including 508 patients treated for at least 6 months and 107 patients treated for approximately 1 year. Patients treated with ibuprofen and famotidine tablet ranged in age from 39 to 80 years (median age 55 years), with 67% female, 79% Caucasian, 18% African-American, and 3% other races. Two randomized, active-controlled clinical studies (Study 301 and Study 303) were conducted for the reduction of the risk of development of ibuprofen-associated, upper gastrointestinal ulcers in patients who required use of ibuprofen, which included 1022 patients on ibuprofen and famotidine tablet and 511 patients on ibuprofen alone. Approximately 15% of patients were on low-dose aspirin. Patients were assigned randomly, in a 2:1 ratio, to treatment with either ibuprofen and famotidine tablet or ibuprofen 800 mg three times a day for 24 consecutive weeks.

Three serious cases of acute renal failure were observed in patients treated with ibuprofen and famotidine tablet in the two controlled clinical trials. All three patients recovered to baseline levels after discontinuation of ibuprofen and famotidine tablet. Additionally, increases in serum creatinine were observed in both treatment arms in the two clinical studies. Many of these patients were taking concomitant diuretics and/or angiotensin-converting enzyme inhibitors, or angiotensin receptor blockers. There were patients with a normal baseline serum creatinine level who developed abnormal values in the controlled trials as presented in Table 1.

Most Commonly Reported Adverse Reactions

The most common adverse reactions (≥2%), from pooled data from the two controlled studies are presented in Table 2.

In controlled clinical studies, the discontinuation rate due to adverse events for patients receiving ibuprofen and famotidine tablet and ibuprofen alone were similar. The most common adverse reactions leading to discontinuation from ibuprofen and famotidine tablet therapy were nausea (0.9%) and upper abdominal pain (0.9%).

There were no differences in types of related adverse reactions seen during maintenance treatment up to 12 months compared to short-term treatment.

6.2 Postmarketing Experience

Ibuprofen

The following adverse reactions have been identified during post-approval use of ibuprofen. Because these reactions are reported voluntarily from a population of uncertain size, it is not always possible to reliably estimate their frequency or establish a causal relationship to drug exposure. These reports are listed below by body system:

Cardiac disorders: myocardial infarction

Gastrointestinal disorders: nausea, vomiting, diarrhea, abdominal pain

General disorders and administrationsite conditions:pyrexia, pain, fatigue, asthenia, chest pain, drug ineffective, edema peripheral

Musculoskeletal and connective tissue disorders:arthralgia

Nervous system disorders: headache, dizziness

Psychiatric disorders: depression, anxiety

Renalandurinary disorders:renal failure acute

Respiratory, thoracic, and mediastinal disorders:dyspnea

Vascular disorders: hypertension

Skin and Appendages:exfoliative dermatitis, Stevens-Johnson Syndrome (SJS), toxic epidermal necrolysis (TEN), and fixed drug eruption (FDE).

Famotidine

The following adverse reactions have been identified during post-approval use of famotidine. Because these reactions are reported voluntarily from a population of uncertain size, it is not always possible to reliably estimate their frequency or establish a causal relationship to drug exposure. These reports are listed below by body system:

Blood and lymphatic system disorders:anemia, thrombocytopenia

Gastrointestinal disorders: nausea, diarrhea, vomiting, abdominal pain

General disorders and administrationsite conditions:pyrexia, condition aggravated, asthenia, drug ineffective, chest pain, fatigue, pain, edema peripheral

Hepatobiliary disorders: hepatic function abnormal

Infections and infestations:pneumonia, sepsis

Investigations: platelet count decreased, aspartate aminotransferase increased, alanine aminotransferase increased, hemoglobin decreased

Metabolism andnutrition disorders:decreased appetite

Nervous system disorders: dizziness, headache

Respiratory, thoracic, and mediastinal disorders:dyspnea

Vascular disorders: hypotension

To report SUSPECTED ADVERSE REACTIONS, contact Camber Pharmaceuticals, Inc., at 1-866-495-8330 or FDA at 1-800-FDA-1088 or www.fda.gov/medwatch.

7 DRUG INTERACTIONS

See Table 3 for clinically significant drug interactions with ibuprofen.

Table 3: Clinically Significant Drug Interactions with Ibuprofen and Famotidine

8 USE IN SPECIFIC POPULATIONS

8.1 Pregnancy

Risk Summary

Use of NSAIDs, including ibuprofen and famotidine tablet, can cause premature closure of the fetal ductus arteriosus and fetal renal dysfunction leading to oligohydramnios and, in some cases, neonatal renal impairment. Because of these risks, limit dose and duration of ibuprofen and famotidine tablet use between about 20 and 30 weeks of gestation and avoid ibuprofen and famotidine tablet use at about 30 weeks of gestation and later in pregnancy (see Clinical Considerations, Data).

There arenoavailable data with ibuprofen and famotidine tablet use in pregnant women to inform a drug-associated risk for major birth defects and miscarriage; however, there are published studies with each individual component of ibuprofen and famotidine tablet.

Ibuprofen

Data from observational studies regarding potential embryofetal risks of NSAID use in women in the first or second trimesters of pregnancy are inconclusive. In animal reproduction studies, there were no clear developmental effects at doses up to 0.4-times the maximum recommended human dose (MRHD) in the rabbit and 0.5-times in the MRHD rat when dosed throughout gestation. In contrast, an increase in membranous ventricular septal defects was reported in rats treated on Gestation Days 9 & 10 with 0.8-times the MRHD. Based on animal data, prostaglandins have been shown to have an important role in endometrial vascular permeability, blastocyst implantation, and decidualization. In animal studies, administration of prostaglandin synthesis inhibitors such as ibuprofen, resulted in increased pre- and post- implantation loss. Prostaglandins also have been shown to have an important role in fetal kidney development. In published animal studies, prostaglandin synthesis inhibitors have been reported to impair kidney development when administered at clinically relevant doses.

Famotidine

Limited published data do not report an increased risk of congenital malformations or other adverse pregnancy effects with use of H2- receptor antagonists, including ibuprofen and famotidine tablet, during pregnancy; however, these data are insufficient to adequately determine a drug-associated risk. Reproductive studies with famotidine have been performed in rats and rabbits at oral doses of up to 2000 and 500 mg/kg/day (approximately 243 and 122 times the recommended human dose, respectively, based on body surface area) and in both species at intravenous (I.V.) doses of up to 200 mg/kg/day, and have revealed no significant evidence of impaired fertility or harm to the fetus due to famotidine.

The estimated background risk of major birth defects and miscarriage for the indicated population is unknown. All pregnancies have a background risk of birth defect, loss, or other adverse outcomes. In the general U.S. population, the estimated background risk of major birth defects and miscarriage in clinically recognized pregnancies is 2-4% and 15-20%, respectively.

Clinical Considerations

Fetal/Neonatal Adverse Reactions

Premature Closure of Fetal Ductus Arteriosus:

Avoid use of NSAIDs in women at about 30 weeks gestation and later in pregnancy, because NSAIDs, including ibuprofen and famotidine tablet, can cause premature closure of the fetal ductus arteriosus (see Data).

Oligohydramnios/Neonatal Renal Impairment

If an NSAID is necessary at about 20 weeks gestation or later in pregnancy, limit the use to the lowest effective dose and shortest duration possible. If ibuprofen and famotidine tablet treatment is needed for a pregnant woman, consider monitoring with ultrasound for oligohydramnios. If oligohydramnios occurs, discontinue ibuprofen and famotidine tablet and follow up according to clinical practice (see Data).

Laboror Delivery

There are no studies on the effects of ibuprofen and famotidine tablet during labor or delivery. In animal studies, NSAIDs, including ibuprofen, inhibit prostaglandin synthesis, cause delayed parturition, and increase the incidence of stillbirth.

Data

Human Data

When used to delay preterm labor, inhibitors of prostaglandin synthesis, including NSAIDs such ibuprofen, may increase the risk of neonatal complications such as necrotizing enterocolitis, patent ductus arteriosus and intracranial hemorrhage. Ibuprofen treatment given in late pregnancy to delay parturition has been associated with persistent pulmonary hypertension, renal dysfunction and abnormal prostaglandin E levels in preterm infants.

Animal Data

Animal reproduction studies have not been conducted with ibuprofen and famotidine tablet.

Ibuprofen

In a published study, female rabbits given 7.5, 20, or 60 mg/kg ibuprofen (0.04, 0.12, or 0.36-times the maximum recommended human daily dose of 3200 mg of ibuprofen based on body surface area) from Gestation Days 1 to 29, no clear treatment-related adverse developmental effects were noted. Doses of 20 and 60 mg/kg were associated with significant maternal toxicity (stomach ulcers, gastric lesions). In the same publication, female rats were administered 7.5, 20, 60, 180 mg/kg ibuprofen (0.02, 0.06, 0.18, 0.54-times the maximum daily dose) did not result in clear adverse developmental effects. Maternal toxicity (gastrointestinal lesions) was noted at 20 mg/kg and above.

In a published study, rats were orally dosed with 300 mg/kg ibuprofen (0.912-times the maximum human daily dose of 3200 mg based on body surface area) during Gestation Days 9 and 10 (critical time points for heart development in rats). Ibuprofen treatment resulted in an increase in the incidence of membranous ventricular septal defects. This dose was associated with significant maternal toxicity including gastrointestinal toxicity. One incidence each of a membranous ventricular septal defect and gastroschisis was noted in fetuses from rabbits treated with 500 mg/kg (3-times the maximum human daily dose) from Gestation Day 9-11.

Famotidine

Reproductive studies with famotidine have been performed in rats and rabbits at oral doses of up to 2000 and 500 mg/kg/day (approximately 243 and 122 times the recommended human dose of 80 mg per day, respectively, based on body surface area) and in both species at intravenous doses of up to 200 mg/kg/day (about 24 and 49 times the recommended human dose of 80 mg per day, respectively, based on body surface area), and have revealed no significant evidence of harm to the fetus due to famotidine. While no direct fetotoxic effects have been observed, sporadic abortions occurring only in mothers displaying marked decreased food intake were seen in some rabbits at oral doses of 200 mg/kg/day (approximately 49 times the recommended human dose of 80 mg per day, respectively, based on body surface area) or higher. Animal reproduction studies are not always predictive of human response.

8.2 Lactation

Risk Summary

No studies have been conducted with the use of ibuprofen and famotidine tablet in lactating women. Limited data from published literature report famotidine is present in human milk in low amounts. Published literature also reports the presence of ibuprofen in human milk in low amounts. No information is available on the effects of famotidine or ibuprofen on milk production or on a breastfed infant. Famotidine is present in the milk of lactating rats (see Data). The developmental and health benefits of breastfeeding should be considered along with the mother’s clinical need for ibuprofen and famotidine tablet and any potential adverse effects on the breastfed infant from ibuprofen and famotidine tablet or from the underlying maternal condition.

Data

Transient growth depression was observed in young rats suckling from mothers treated with maternotoxic doses of at least 300 times the usual human dose of famotidine.

8.3 Females and Males of Reproductive Potential

Infertility

Females

Based on the mechanism of action, the use of prostaglandin-mediated NSAIDs, including ibuprofen and famotidine tablet, may delay or prevent rupture of ovarian follicles, which has been associated with reversible infertility in some women. Published animal studies have shown that administration of prostaglandin synthesis inhibitors has the potential to disrupt prostaglandin-mediated follicular rupture required for ovulation. Small studies in women treated with NSAIDs have also shown a reversible delay in ovulation. Consider withdrawal of NSAIDs, including ibuprofen and famotidine tablet, in women who have difficulties conceiving or who are undergoing investigation of infertility.

8.4 Pediatric Use

Safety and effectiveness of ibuprofen and famotidine tablet in pediatric patients have not been established.

8.5 Geriatric Use

Elderly patients, compared to younger patients, are at greater risk for NSAID-associated serious cardiovascular, gastrointestinal, and/or renal adverse reactions. If the anticipated benefit for the elderly patient outweighs these potential risks, start dosing at the low end of the dosing range, and monitor patients for adverse effects [see Warnings and Precautions (5.1, 5.2, 5.4, 5.7, 5.16)].

The clinical trials primarily enrolled patients less than 65 years of age. Of the 1022 patients in clinical studies of ibuprofen and famotidine tablet, 18% (249 patients) were 65 years of age or older. Efficacy results in patients who are greater than or equal to 65 years of age are summarized in the CLINICAL STUDIES section [see Clinical Studies (14)].

Famotidine is known to be substantially excreted by the kidney, and the risk of toxic reactions to this drug may be greater in patients with impaired renal function. Because elderly patients are more likely to have decreased renal function, care should be taken in dose selection and adjusting dose interval, and it may be useful to monitor renal function [see Warnings and Precautions (5.7)].

8.6 Renal Insufficiency

In adult patients with renal insufficiency (creatinine clearance < 50 mL/min), the elimination half-life of famotidine is increased. Since CNS adverse effects have been reported in patients with creatinine clearance < 50 mL/min and the dosage of the famotidine component in ibuprofen and famotidine tablet is fixed, ibuprofen and famotidine tablet is not recommended in these patients [see Warnings and Precautions (5.7)].

10 OVERDOSAGE

Symptoms following acute NSAID overdosages have been typically limited to lethargy, drowsiness, nausea, vomiting, and epigastric pain, which have been generally reversible with supportive care. Gastrointestinal bleeding has occurred. Hypertension, acute renal failure, respiratory depression, and coma have occurred, but were rare [see Warnings and Precautions (5.1, 5.2, 5.5, 5.7, 5.9)].

No data are available with regard to overdose of ibuprofen and famotidine tablet. Findings related to the individual active substances are listed below.

Ibuprofen

Approximately 1 1/2 hours after the reported ingestion of from 7 to 10 ibuprofen tablets (400 mg), a 19-month-old child weighing 12 kg was seen in the hospital emergency room, apneic and cyanotic, responding only to painful stimuli. This type of stimulus, however, was sufficient to induce respiration. Oxygen and parenteral fluids were given; a greenish-yellow fluid was aspirated from the stomach with no evidence to indicate the presence of ibuprofen. Two hours after ingestion the child's condition seemed stable; she still responded only to painful stimuli and continued to have periods of apnea lasting from 5 to 10 seconds. She was admitted to intensive care and sodium bicarbonate was administered as well as infusions of dextrose and normal saline. By 4 hours post-ingestion she could be aroused easily, sit by herself, and respond to spoken commands. Blood level of ibuprofen was 102.9 μg/mL approximately 8.5 hours after accidental ingestion. At 12 hours she appeared to be completely recovered.

In two other reported cases where children (each weighing approximately 10 kg) accidentally, acutely ingested approximately 120 mg/kg, there were no signs of acute intoxication or late sequelae. Blood level in one child 90 minutes after ingestion was 700 μg/mL — about 10 times the peak levels seen in absorption-excretion studies.

A 19-year-old male who had taken 8,000 mg of ibuprofen over a period of a few hours complained of dizziness, and nystagmus was noted. After hospitalization, parenteral hydration and 3 days bed rest, he recovered with no reported sequelae.

Famotidine

The adverse reactions in overdose cases are similar to the adverse reactions encountered in normal clinical experience. Oral doses of up to 640 mg/day have been given to adult patients with pathological hypersecretory conditions with no serious adverse effects.

Manage patients with symptomatic and supportive care following an NSAID overdosage, including ibuprofen and famotidine tablet overdose. There are no specific antidotes. Consider emesis and/or activated charcoal (60 to 100 grams in adults, 1 to 2 grams per kg of body weight in pediatric patients) and/or osmotic cathartic in symptomatic patients seen within four hours of ingestion or in patients with a large overdosage (5 to 10 times the recommended dose). Forced diuresis, alkalinization of urine, hemodialysis, or hemoperfusion may not be useful due to high protein binding.

If over-exposure occurs, call your poison control center at 1-800-222-1222 for current information on the management of poisoning or over-exposure.

11 DESCRIPTION

Ibuprofen and famotidine is supplied as a tablet for oral administration which combines the nonsteroidal anti-inflammatory drug, ibuprofen, and the histamine H2-receptor antagonist, famotidine.

Ibuprofen is (±)-2-(p-isobutylphenyl)propionic acid. Its chemical formula is C13H18O2 and molecular weight is 206.28. Ibuprofen is a white powder that is very slightly soluble in water (<1 mg/mL) and readily soluble in organic solvents such as ethanol and acetone. Its structural formula is:

Famotidine is N'-(aminosulfonyl)-3-[[[2-[(diaminomethylene)amino]-4-thiazolyl]methyl]thio]propanimidamide. Its chemical formula is C8H15N7O2S3 and molecular weight is 337.43. Famotidine is a white to pale yellow crystalline compound that is freely soluble in glacial acetic acid, slightly soluble in methanol, very slightly soluble in water, and practically insoluble in ethanol. Its structural formula is:

Each ibuprofen and famotidine tablet contains ibuprofen (800 mg) and famotidine, USP (26.6 mg). The inactive ingredients in ibuprofen and famotidine tablet include: microcrystalline cellulose, pregelatinized starch, silicon dioxide, magnesium stearate, Hydroxy Propyl Methyl Cellulose, Glycerin, croscarmellose sodium, FD&C Blue#1, talc, povidone, FD&C Blue#2.

12 CLINICAL PHARMACOLOGY

12.1 Mechanism of Action

Ibuprofen and famotidine tablet is a fixed-combination tablet of ibuprofen and famotidine. The ibuprofen component has analgesic, anti-inflammatory, and antipyretic properties. The mechanism of action of the ibuprofen component of ibuprofen and famotidine tablet, like that of other NSAIDs, is not completely understood but involves inhibition of cyclooxygenase (COX-1 and COX-2).

Ibuprofen is a potent inhibitor of prostaglandin synthesis in vitro. Ibuprofen concentrations reached during therapy have produced in vivoeffects. Prostaglandins sensitize afferent nerves and potentiate the action of bradykinin in inducing pain in animal models. Prostaglandins are mediators of inflammation. Because ibuprofen is an inhibitor of prostaglandin synthesis, its mode of action may be due to an increase of prostaglandins in peripheral tissues.

Famotidine is a competitive inhibitor of histamine H2-receptors. The primary clinically important pharmacologic activity of famotidine is inhibition of gastric secretion. Both the acid concentration and volume of gastric secretion are suppressed by famotidine, while changes in pepsin secretion are proportional to volume output.

Systemic effects of famotidine in the CNS, cardiovascular, respiratory, or endocrine systems were not noted in clinical pharmacology studies. Also, no antiandrogenic effects were noted. Serum hormone levels, including prolactin, cortisol, thyroxine (T4), and testosterone, were not altered after treatment with famotidine.

12.2 Pharmacodynamics

In a healthy volunteer study, ibuprofen 400 mg given once daily, administered 2 hours prior to immediate-release aspirin (81 mg) for 6 days, showed an interaction with the antiplatelet activity of aspirin as measured by % serum thromboxane B2 (TxB2) inhibition at 24 hours following the day-6 aspirin dose [53%]. An interaction was still observed, but minimized, when ibuprofen 400 mg given once-daily was administered as early as 8 hours prior to the immediate-release aspirin dose [90.7%]. However, there was no interaction with the antiplatelet activity of aspirin when ibuprofen 400 mg, given once daily, was administered 2 hours after (but not concomitantly, 15 min, or 30 min after) the immediate-release aspirin dose [99.2%].

In another study, where immediate-release aspirin 81 mg was administered once daily with ibuprofen 400 mg given three times daily (1, 7, and 13 hours post-aspirin dose) for 10 consecutive days, the mean % serum thromboxane B2 (TxB2) inhibition suggested no interaction with the antiplatelet activity of aspirin [98.3%]. However, there were individual subjects with serum TxB2 inhibition below 95%, with the lowest being 90.2%.

When a similarly designed study was conducted with enteric-coated aspirin, where healthy subjects were administered enteric-coated aspirin 81 mg once daily for 6 days and ibuprofen 400 mg three times daily (2, 7, and 12 h post-aspirin dose) for 6 days, there was an interaction with the antiplatelet activity at 24 hours following the day-6 aspirin dose [67%] [see Drug Interactions (7)].

12.3 Pharmacokinetics

Absorption

Ibuprofen and famotidine are rapidly absorbed after a single dose administration of ibuprofen and famotidine tablet. Mean Cmax values for ibuprofen are 45 µg/mL and are reached approximately 1.9 hours after oral administration of ibuprofen and famotidine tablet. The Cmax and AUC0-24hours values for the 800 mg of ibuprofen contained in a ibuprofen and famotidine tablet are bioequivalent to the values for 800 mg of ibuprofen administered alone. Cmax values for famotidine were 61 ng/mL and are reached at approximately 2 hours after oral administration of ibuprofen and famotidine tablet.

A high-fat meal reduced famotidine Cmax and AUC by approximately by 15% and 11%, respectively, and reduced ibuprofen AUC by approximately 14% but did not change Cmax. Food delayed famotidine Tmax and ibuprofen Tmax by approximately 1 hour and 0.2 hour, respectively.

Distribution

Ibuprofen is extensively bound to plasma proteins.

Fifteen to 20% of famotidine in plasma is protein bound.

Elimination

Metabolism

The only metabolite of famotidine identified in man is the S-oxide.

Excretion

Ibuprofen is eliminated from the systemic circulation with a mean half-life (t1/2) value of 2 hours following administration of a single dose of ibuprofen and famotidine tablet.

Ibuprofen is rapidly metabolized and eliminated in the urine. The excretion of ibuprofen is virtually complete 24 hours after the last dose.

Studies have shown that following ingestion of the drug, 45% to 79% of the dose was recovered in the urine within 24 hours as metabolite A (25%), (+)-2-[p-(2-hydroxymethyl-propyl) phenyl] propionic acid and metabolite B (37%), (+)-2-[p-(2-carboxypropyl)phenyl] propionic acid; the percentages of free and conjugated ibuprofen were approximately 1% and 14%, respectively.

Famotidine is eliminated from the systemic circulation with a mean t1/2value of 4 hours following administration of a single dose of ibuprofen and famotidine tablet.

Famotidine is eliminated by renal (65-70%) and metabolic (30-35%) routes. Renal clearance is 250-450 mL/min, indicating some tubular excretion. Twenty-five to 30% of an oral dose and 65-70% of an intravenous dose are recovered in the urine as unchanged compound.

Specific Populations

Pediatrics: The pharmacokinetics of ibuprofen or famotidine after administration of ibuprofen and famotidine tablet have not been evaluated in a pediatric population considering the doses of ibuprofen and famotidine in ibuprofen and famotidine tablet are targeted for use in an adult population.

Hepatic impairment: The effects of hepatic impairment on the pharmacokinetics of ibuprofen or famotidine after administration of ibuprofen and famotidine tablet have not been evaluated [see Warnings and Precautions (5.4)].

Renal impairment: There is a close relationship between creatinine clearance values and the elimination t1/2 of famotidine, which is a component of ibuprofen and famotidine tablets. In patients with creatinine clearance <50 mL/min, the elimination t1/2of famotidine is increased and may exceed 20 hours. Therefore, ibuprofen and famotidine tablet is not recommended in patients with creatinine clearance < 50 mL/min [see Warnings and Precautions (5.7)].

Drug Interaction Studies

Co-administration of ibuprofen (800 mg) and famotidine (40 mg) increased ibuprofen Cmax by 15.6% but did not affect its AUC, and increased famotidine AUC and Cmax by 16% and 22%, respectively.

Aspirin: When NSAIDs were administered with aspirin, the protein binding of NSAIDs were reduced, although the clearance of free NSAID was not altered. The clinical significance of this interaction is not known. See Table 3 for clinically significant drug interactions of NSAIDs with aspirin [see Drug Interaction (7)].

Probenecid, an inhibitor of Organic Aniton Transporter 1 (OAT1) and OAT3

In vitrostudies indicate that famotidine is a substrate for OAT1 and OAT3. Following coadministration of probenecid (1500 mg) with a single oral 20 mg dose of famotidine in 8 healthy subjects, the serum AUC0-10h of famotidine increased from 424 to 768 ng×hr/mL and the maximum serum concentration (Cmax) increased from 73 to 113 ng/mL. Renal clearance, urinary excretion rate and amount of famotidine excreted unchanged in urine were decreased. The clinical relevance of this interaction is unknown.

Metformin: Famotidine is a selective inhibitor of multidrug and toxin extrusion transporter 1 (MATE-1) but no clinical significant interaction with metformin, a substrate for MATE-1, was observed.

13 NONCLINICAL TOXICOLOGY

13.1 Carcinogenesis, Mutagenesis, and Impairment of Fertility

Carcinogenesis

Studies to evaluate the potential effects of ibuprofen and famotidine tablet on carcinogenicity, mutagenicity, or impairment of fertility have not been conducted.

In a 106-week study in rats and a 92-week study in mice, famotidine was given at oral doses of up to 2000 mg/kg/day (approximately 122 and 243 times the recommended human dose, respectively, based on body surface area). There was no evidence of carcinogenic potential for famotidine.

Mutagenesis

Famotidine was negative in the microbial mutagen test (Ames test) using Salmonellatyphimuriumand Escherichia coliwith or without rat liver enzyme activation at concentrations up to 10,000 µg/plate. In in vivomouse micronucleus test and a chromosomal aberration test with famotidine, no evidence of a mutagenic effect was observed.

In published studies, ibuprofen was not mutagenic in the in vitrobacterial reverse mutation assay (Ames assay).

Impairment of Fertility

In studies of famotidine in rats at oral doses of up to 2000 mg/kg/day (approximately 243 times the recommended human dose, based on body surface area), fertility and reproductive performance were not affected.

In a published study, dietary administration of ibuprofen to male and female rats 8-weeks prior to and during mating at dose levels of 20 mg/kg (0.06-times the MRHD based on body surface area comparison) did not impact male or female fertility or litter size.

In other studies, adult mice were administered ibuprofen intraperitoneally at a dose of 5.6 mg/kg/day (0.0085-times the MRHD based on body surface area comparison) for 35 or 60 days in males and 35 days in females. There was no effect on sperm motility or viability in males but decreased ovulation was reported in females.

14 CLINICAL STUDIES

Two multicenter, double-blind, active-controlled, randomized, 24-week studies of ibuprofen and famotidine tablet were conducted in patients who were expected to require daily administration of an NSAID for at least the coming 6 months for conditions such as the following: osteoarthritis, rheumatoid arthritis, chronic low back pain, chronic regional pain syndrome, and chronic soft tissue pain. Patients were assigned randomly, in approximately a 2:1 ratio, to treatment with either ibuprofen and famotidine tablet or ibuprofen (800 mg) three times a day for 24 consecutive weeks. A total of 1533 patients were enrolled and ranged in age from 39 to 80 years (median age 55 years) with 68% females. Race was distributed as follows: 79% Caucasian, 18% African-American, and 3% Other. Approximately 15% of the patients in Studies 301 and 303 were taking concurrent low-dose aspirin (less than or equal to 325 mg daily), 18% were 65 years of age or older, and 6% had a history of previous upper gastrointestinal ulcer. Although H. pylori status was negative at baseline, H. pylori status was not reassessed during the trials.

Studies 301 and 303 compared the incidence of upper gastrointestinal (gastric and/or duodenal) ulcer formation in a total 930 patients taking ibuprofen and famotidine tablet and 452 patients taking ibuprofen only, either as a primary or secondary endpoint. In both trials, ibuprofen and famotidine was associated with a statistically significantly reduction in the risk of developing upper gastrointestinal ulcers compared to taking ibuprofen only during the 6 month study period. The data are presented below in Tables 4 and 5. Two analyses for each endpoint were conducted. In one analysis patients who terminated early, without an endoscopic evaluation within 14 days of their last dose of study drug, were classified as not having an ulcer. In the second analysis, those patients were classified as having an ulcer. Both analyses exclude patients who terminated study prior to the first scheduled endoscopy at 8 weeks.

Subgroup analyses of patients who used low-dose aspirin (less than or equal to 325 mg daily), were 65 years and older, or had a prior history of gastrointestinal ulcer are summarized as follows:

Of the 1022 patients in clinical studies of ibuprofen and famotidine tablet, 15% (213 patients) used low-dose aspirin and the results were consistent with the overall findings of the study. In these clinical studies 16% of patients who used low-dose aspirin who were treated with ibuprofen and famotidine tablet developed an upper gastrointestinal ulcer compared to 35% of those patients who received only ibuprofen.

The clinical trials primarily enrolled patients less than 65 years without a prior history of gastrointestinal ulcer. Of the 1022 patients in clinical studies of ibuprofen and famotidine tablet, 18% (249 patients) were 65 years of age or older. In these clinical studies, 23% of patients 65 years of age and older who were treated with ibuprofen and famotidine tablet developed an upper gastrointestinal ulcer compared to 27% of those patients who received only ibuprofen [see Use in Specific Populations (8.5)].

Of the 1022 patients in clinical studies of ibuprofen and famotidine tablet, 6% had a prior history of gastrointestinal ulcer. In these clinical studies, 25% of patients with a prior history of gastrointestinal ulcer who were treated with ibuprofen and famotidine tablet developed an upper gastrointestinal ulcer compared to 24% of those patients who received only ibuprofen.

16 HOW SUPPLIED/STORAGE AND HANDLING

Ibuprofen and famotidine tablets, 800 mg/26.6 mg, are Blue/Light blue coated Modified Oval shaped tablets debossed with T396 on one side and an engraved circle on the other side and supplied as:

NDC Number | Size
85509-1315-3 | Bottle of 30 tablets
85509-1315-6 | Bottle of 60 tablets
85509-1315-9 | Bottle of 90 tablets

Storage

Store at 25°C (77°F); excursions permitted to 15°C - 30°C (59°F - 86°F). [See USP Controlled Room Temperature]

Repackaged/Relabeled by:
PHOENIX RX LLC
Hatboro, PA 19040

17 PATIENT COUNSELING INFORMATION

Advise the patient to read the FDA-approved patient labeling (Medication Guide).

Inform patients, families, or caregivers of the following before initiating therapy with ibuprofen and famotidine tablet and periodically during the course of ongoing therapy.

Cardiovascular Thrombotic Events

Advise patients to be alert for the symptoms of cardiovascular thrombotic events, including chest pain, shortness of breath, weakness, or slurring of speech, and to report any of these symptoms to their health care provider immediately [see Warnings and Precautions (5.1)].

Gastrointestinal Bleeding, Ulceration, and Perforation

Advise patients to report symptoms of ulcerations and bleeding, including epigastric pain, dyspepsia, melena, and hematemesis to their health care provider. In the setting of concomitant use of low-dose aspirin for cardiac prophylaxis, inform patients of the increased risk for and the signs and symptoms of GI bleeding [see Warnings and Precautions (5.2)].

Hepatotoxicity

Inform patients of the warning signs and symptoms of hepatotoxicity (e.g., nausea, fatigue, lethargy, pruritus, jaundice, right upper quadrant tenderness, and “flu-like” symptoms). If these occur, instruct patients to stop ibuprofen and famotidine tablet and seek immediate medical therapy [see Warnings and Precautions (5.4) ].

Heart Failure and Edema

Advise patients to be alert for the symptoms of congestive heart failure including shortness of breath, unexplained weight gain, or edema and to contact their health care provider if such symptoms occur [see Warnings and Precautions (5.6)].

Anaphylactic Reactions

Inform patients of the signs of an anaphylactic reaction (e.g., difficulty breathing, swelling of the face or throat). Instruct patients to seek immediate emergency help if these occur [see Contraindications (4), Warnings and Precautions (5.8)].

Serious Skin Reactions, including DRESS

Advise patients to stop taking ibuprofen and famotidine tablet immediately if they develop any type of rash or fever and contact their health care provider as soon as possible [see Warnings and Precautions (5.11, 5.12)].

Infertility

Advise females of reproductive potential who desire pregnancy that NSAIDs, including ibuprofen and famotidine tablet, may be associated with a reversible delay in ovulation [see Use in Specific Populations (8.3)].

Fetal Toxicity

Inform pregnant women to avoid use of ibuprofen and famotidine tablet and other NSAIDs starting at 30 weeks gestation because of the risk of the premature closure of the fetal ductus arteriosus. If treatment with ibuprofen and famotidine tablet is needed for a pregnant woman between about 20 to 30 weeks gestation, advise her that she may need to be monitored for oligohydramnios [see Warnings and Precautions (5.13) and Use in Specific Populations (8.1)].

Avoid Concomitant Use of NSAIDs

Inform patients that the concomitant use of ibuprofen and famotidine tablet with other NSAIDs or salicylates (e.g., diflunisal, salsalate) is not recommended due to the increased risk of gastrointestinal toxicity, and little or no increase in efficacy [see Warnings and Precautions (5.2, 5.17), Drug Interactions (7)]. Alert patients that NSAIDs may be present in the “over the counter” medications for treatment of colds, fever or insomnia.

Useof NSAIDs and Low-Dose Aspirin

Inform patients not to use low-dose aspirin concomitantly with ibuprofen and famotidine tablet until they talk to their health care provider [see Drug Interactions (7)].

Nephrotoxicity

Patients should be monitored for development of nephrotoxicity (e.g., azotemia, hypertension, and /or proteinuria). If these patients should be instructed to stop therapy and seek immediate medical therapy.

Creatinine Clearance

Ibuprofen and famotidine tablet is not recommended in patients with creatinine clearance <50 mL/min because of seizures, delirium, coma and other CNS effect.

Taking ibuprofen and famotidine tablet

Inform patients that ibuprofen and famotidine tablets should be swallowed whole, and should not be cut to supply a lower dose. Advise patient not to chew, divide, or crush tablets [see Dosage and Administration (2)].

Patients should be instructed that if a dose is missed, it should be taken as soon as possible. However, if the next scheduled dose is due, the patient should not take the missed dose, and should be instructed to take the next dose on time. Patients should be instructed not to take 2 doses at one time to make up for a missed dose.

Manufactured by:

Ascent Pharmaceuticals, Inc.

Central Islip, NY 11722

Manufactured for:

Camber Pharmaceuticals, Inc.

Piscataway, NJ 08854

Rev: 07/24

Medication Guide

IBUPROFEN and FAMOTIDINE

(eye-BYOO-proe-fen and fa-MOE-ti-deen)

tablets, for oral use

What is the most important information I should know about ibuprofen and famotidine tablet?

Ibuprofen and famotidine tablet can cause serious side effects including:

You should take ibuprofen and famotidine tablet exactly as prescribed, at the lowest dose possible and for the shortest time needed. Ibuprofen and famotidine tablet contains a non-steroidal anti-inflammatory drug NSAID (ibuprofen). Do notuse ibuprofen and famotidine tablet with other medicines to lessen pain or fever or with other medicines for colds or sleeping problems without talking to your healthcare provider first, because they may contain an NSAID also.

Ibuprofen and famotidine tablet may help your acid-related symptoms, but you could still haveserious stomach problems.Talk with your healthcare provider.

Ibuprofen and famotidine tablet contains ibuprofen, an NSAID and famotidine, a histamine H2-receptor blocker medicine.

What is ibuprofen and famotidine tablet?

Ibuprofen and famotidine tablet is a prescription medicine used to:

- relieve the signs and symptoms of rheumatoid arthritis and osteoarthritis.
- decrease the risk of developing ulcers of the stomach and upper intestines (upper gastrointestinal ulcers) in people taking ibuprofen for rheumatoid arthritis and osteoarthritis.

It is not known if ibuprofen and famotidine tablet is safe and effective in children.

Do not take ibuprofen and famotidine tablet:

- if you are allergic to ibuprofen, famotidine, any other histamine H2-receptor blocker, or any of the ingredients in ibuprofen and famotidine tablet. See the end of this Medication Guide for a complete list of ingredients.
- if you have had an asthma attack, hives, or other allergic reaction with aspirin or any other NSAIDs.
- right before or after heart bypass surgery.

Before taking ibuprofen and famotidine tablet, tell your healthcare provider about all of your medical conditions, including if you:

- have liver or kidney problems.
- have high blood pressure.
- have heart problems.
- have asthma.
- have bleeding problems.
- are pregnant or plan to become pregnant. Taking ibuprofen and famotidine tablet at about 20 weeks of pregnancy or later may harm your unborn baby. If you need to take ibuprofen and famotidine tablet when you are between 20 and 30 weeks of pregnancy, your healthcare provider may need to monitor the amount of fluid in your womb around your baby. You should not take ibuprofen and famotidine tablet after about 30 weeks of pregnancy.
- are breastfeeding or plan to breast feed. Ibuprofen and famotidine can pass into your breast milk. Talk to your healthcare provider about the best way to feed your baby if you take ibuprofen and famotidine tablet.

Tell your healthcare provider about all of the medicines you take, including prescription and over-the-counter medicines, vitamins and herbal supplements. Ibuprofen and famotidine tablet and some other medicines can interact with each other and cause serious side effects. Do not start taking any new medicine without talking to your healthcare provider first.

How should I take ibuprofen and famotidine tablet?

- Take ibuprofen and famotidine tablet exactly as your healthcare provider tells you to take it.
- Your healthcare provider will tell you how many ibuprofen and famotidine tablet to take and when to take it.
- Do not change your dose or stop ibuprofen and famotidine tablet without first talking to your healthcare provider.
- Swallow ibuprofen and famotidine tablets whole with liquid. Do not split, chew, crush or dissolve the ibuprofen and famotidine tablet. Tell your healthcare provider if you cannot swallow the tablet whole. You may need a different medicine.
- If you forget to take your dose of ibuprofen and famotidine tablet, take it as soon as you remember. If it is almost time for your next dose, do not take the missed dose. Take the next dose on time. Do not take 2 doses at one time to make up for a missed dose.
- You should not take an ibuprofen tablet and famotidine tablet together instead of taking ibuprofen and famotidine tablet, because they will not work in the same way.

What are the possible side effects of ibuprofen and famotidine tablet?

Ibuprofen and famotidine tablet can cause serious side effects, including:

See “What is the most important information I should know about ibuprofen and famotidine tablet?

Other side effects of ibuprofen and famotidine tablet include: stomach pain, constipation, diarrhea, gas, heartburn, nausea, vomiting, and dizziness.

Get emergency help right away if you get any of the following symptoms:

Stop taking ibuprofen and famotidine tablet and call your healthcare provider right away if you get any of the following symptoms:

If you take too much ibuprofen and famotidine tablet, call your poison control center at 1-800-222-1222.

These are not all the possible side effects of ibuprofen and famotidine tablet. Call your doctor for medical advice about side effects. You may report side effects to FDA at 1-800-FDA-1088.

Other information about NSAIDs

- Aspirin is an NSAID but it does not increase the chance of a heart attack. Aspirin can cause bleeding in the brain, stomach, and intestines. Aspirin can also cause ulcers in the stomach and intestines.
- Some NSAIDs are sold in lower doses without a prescription (over-the-counter). Talk to your healthcare provider before using over-the-counter NSAIDs for more than 10 days.

General information about the safe and effective use of ibuprofen and famotidine tablet

Medicines are sometimes prescribed for purposes other than those listed in a Medication Guide. Do not use ibuprofen and famotidine tablet for a condition for which it was not prescribed. Do not give ibuprofen and famotidine tablet to other people, even if they have the same symptoms that you have. It may harm them.

You can ask your pharmacist or healthcare provider for information about NSAIDs that is written for health professionals.

What are the ingredients in ibuprofen and famotidine tablet?

Active ingredients:ibuprofen and famotidine

Inactive ingredients:microcrystalline cellulose, pregelatinized starch, silicon dioxide, magnesium stearate, Hydroxy Propyl Methyl Cellulose, Glycerin, croscarmellose sodium, FD&C Blue#1, talc, povidone, FD&C Blue#2.

For more information, call Camber Pharmaceuticals, Inc., at 1-866-495-8330.

Medication Guide available at http://camberpharma.com/medication-guides

Manufactured by:

Ascent Pharmaceuticals, Inc.

Central Islip, NY 11722

Manufactured for:

Camber Pharmaceuticals, Inc.

Piscataway, NJ 08854

This Medication Guide has been approved by the U.S. Food and Drug Administration. Revised: 03/23